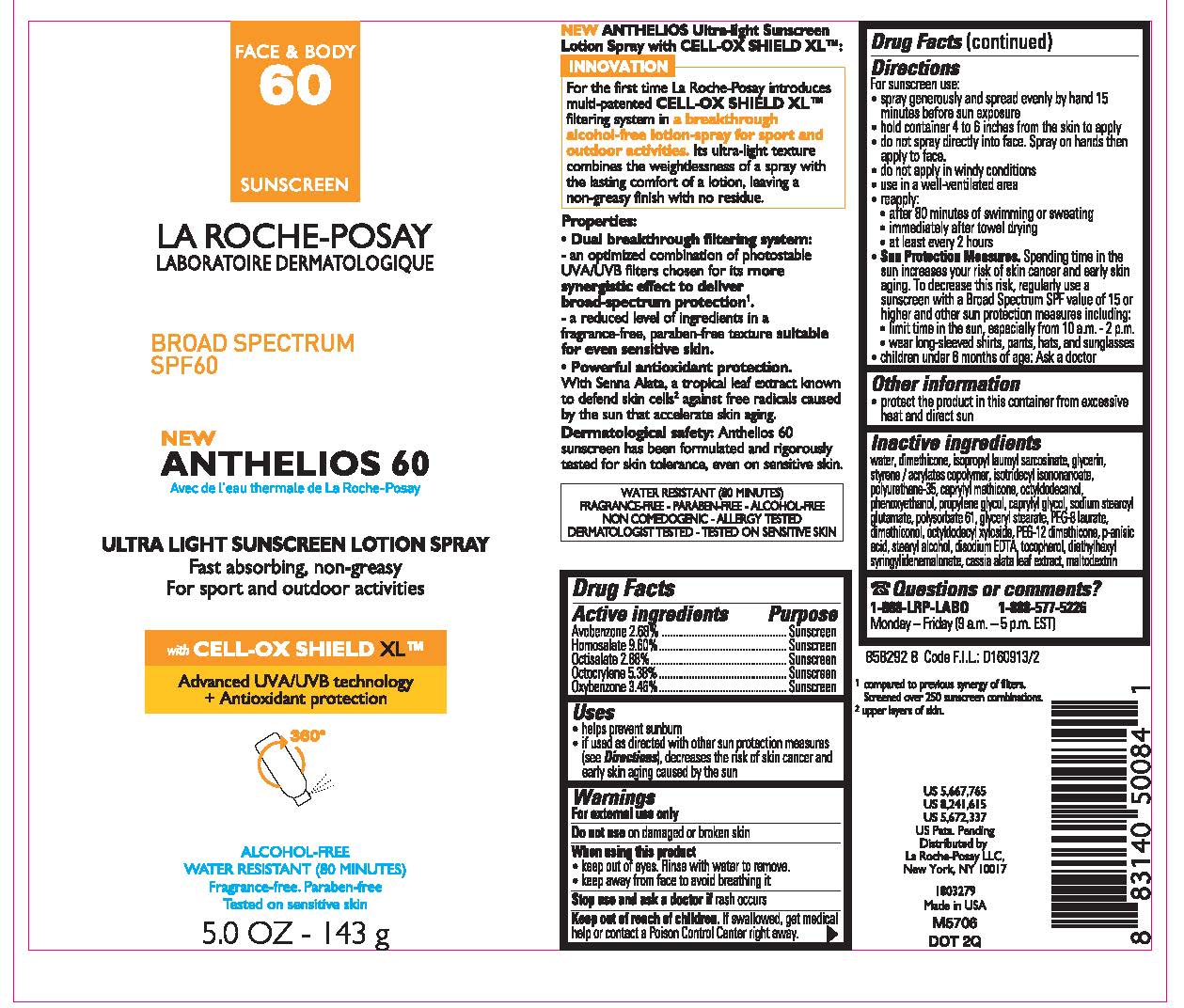 DRUG LABEL: La Roche Posay Laboratoire Dermatologique Anthelios 60 Ultra Light Sunscreen Broad Spectrum SPF 60 Water Resistant 80 Minutes
NDC: 49967-008 | Form: SPRAY
Manufacturer: L'Oreal USA Products Inc
Category: otc | Type: HUMAN OTC DRUG LABEL
Date: 20231231

ACTIVE INGREDIENTS: Avobenzone 26.8 mg/1 g; Homosalate 96 mg/1 g; Octisalate 28.8 mg/1 g; Octocrylene 53.8 mg/1 g; Oxybenzone 34.6 mg/1 g
INACTIVE INGREDIENTS: WATER; DIMETHICONE; ISOPROPYL LAUROYL SARCOSINATE; GLYCERIN; STYRENE/ACRYLAMIDE COPOLYMER (500000 MW); ISOTRIDECYL ISONONANOATE; CAPRYLYL TRISILOXANE; OCTYLDODECANOL; PHENOXYETHANOL; PROPYLENE GLYCOL; CAPRYLYL GLYCOL; SODIUM STEAROYL GLUTAMATE; POLYSORBATE 61; GLYCERYL MONOSTEARATE; PEG-8 LAURATE; DIMETHICONOL (2000 CST); OCTYLDODECYL XYLOSIDE; PEG-12 DIMETHICONE; p-ANISIC ACID; STEARYL ALCOHOL; EDETATE DISODIUM; TOCOPHEROL; DIETHYLHEXYL SYRINGYLIDENEMALONATE; SENNA ALATA LEAF; MALTODEXTRIN

Drug Facts

Active ingredients

Avobenzone 2.68%

Homosalate 9.6%

Octisalate 2.88%

Octocrylene 5.38%

Oxybenzone 3.46%

Purpose

Sunscreen

Uses

- helps prevent sunburn
- if used as directed with other sun protection measures (see Directions), decreases the risk of skin cancer and early skin aging caused by the sun

Warnings

For external use only

Do not use

on damaged or broken skin

When using this product

- keep out of eyes. Rinse with water to remove.
- keep away from face to avoid breathing it

Stop use and ask a doctor if

rash occurs

Keep out of reach of children.

If swallowed, get medical help or contact a Poison Control Center right away.

Directions

For sunscreen use:

● spray generously and spread evenly by hand 15 minutes before sun exposure

● hold container 4 to 6 inches from the skin to apply

● do not spray directly into face. Spray on hands then apply to face.

● do not apply in windy conditions

● use in a well-ventilated area

● reapply:

● after 80 minutes of swimming or sweating

● immediately after towel drying

● at least every 2 hours

● Sun Protection Measures. Spending time in the sun increases your risk of skin cancer and early skin aging. To decrease this risk, regularly use a sunscreen with a Broad Spectrum SPF value of 15 or higher and other sun protection measures including:

● limit time in the sun, especially from 10 a.m. – 2 p.m.

● wear long-sleeved shirts, pants, hats, and sunglasses

● children under 6 months of age: Ask a doctor

Other information

protect the product in this container from excessive heat and direct sun

Inactive ingredients

water, dimethicone, isopropyl lauroyl sarcosinate, glycerin, styrene/acrylates copolymer, isotridecyl isononanoate, polyurethane-35, caprylyl methicone, octyldodecanol, phenoxyethanol, propylene glycol, caprylyl glycol, sodium stearoyl glutamate, polysorbate 61, glyceryl stearate, PEG-8 laurate, dimethiconol, octyldodecyl xyloside, PEG-12 dimethicone, p-anisic acid, stearyl alcohol, disodium EDTA, tocopherol, diethylhexyl syringylidenemalonate, cassia alata leaf extract, maltodextrin

Questions or comments?

1-888-LRP-LABO 1-888-577-5226

Monday - Friday (9 a.m. - 5 p.m. EST)